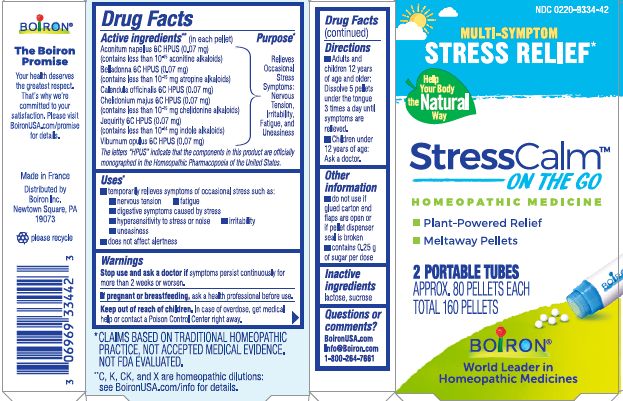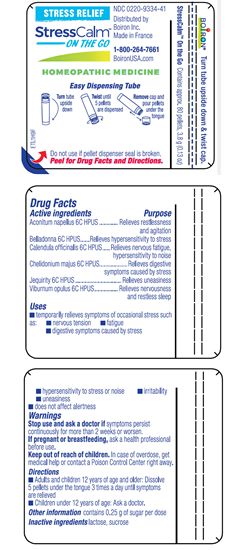 DRUG LABEL: StressCalm
NDC: 0220-9334 | Form: PELLET
Manufacturer: Boiron
Category: homeopathic | Type: HUMAN OTC DRUG LABEL
Date: 20230405

ACTIVE INGREDIENTS: ACONITUM NAPELLUS 6 [hp_C]/1 1; ATROPA BELLADONNA 6 [hp_C]/1 1; CHELIDONIUM MAJUS 6 [hp_C]/1 1; CALENDULA OFFICINALIS FLOWERING TOP 6 [hp_C]/1 1; ABRUS PRECATORIUS SEED 6 [hp_C]/1 1; VIBURNUM OPULUS BARK 6 [hp_C]/1 1
INACTIVE INGREDIENTS: LACTOSE, UNSPECIFIED FORM; SUCROSE

StressCalm Pellets

Active Ingredients** (in each pellet)

Aconitum napellus 6C HPUS (0.07 mg) (contains less than 10^-15 mg aconitine alkaloids)

Belladonna 6C HPUS (0.07 mg) (contains less than 10^-15 mg atropine alkaloids)

Calendula officinalis 6C HPUS (0.07 mg)

Chelidonium majus 6C HPUS (0.07 mg) (contains less than 10^-15 mg chelidonine alkaliods)

Jequirity 6C HPUS (0.07 mg) (contains less than 10^-14 indole alkaloids)

Viburnum opulus 6C HPUS (0.07 mg)

The letters "HPUS" indicate that the components in this product are officially monographed in the Homeopathic Pharmacopoeia of the United States.

Purpose*

Relieves Occasional Stress Symptoms: Nervous Tension, Irritability, Fatigue, and Uneasiness

Uses*

Temporarily relieves symptoms of occasional stress such as:

nervous tension

fatigue

digestive symptoms caused by stress

hypersensitivity to stress or noise

irritability

uneasiness

does not affect alertness

Stop use and ask a doctor if symptoms persist continuously for more than 2 weeks or worsen.

PREGNANCY OR BREAST FEEDING

If pregnant or breastfeeding, ask a health professional before use.

Keep out of reach of children. In case of overdoes, get medical help or contact a Poison Control Center right away.

DOSAGE AND ADMINISTRATION

- Adults and children 12 years of age and older: Dissolve 5 pellets under the tongue 3 times a day until symptoms are relieved.
- Children under 12 years of age: Ask a doctor.

INACTIVE INGREDIENT

lactose, sucrose

do not use if glued carton end flaps are open or if pellet dispenser seal is broken

contains 0.25 g of sugar per dose

Multi-Symptom

Stress Relief*

Plant-powered Relief

Meltaway Pellets

2 PORTABLE TUBES

APPROX. 80 PELLETS EACH

TOTAL 160 PELLETS

Tube - Contains approx. 80 pellets, 3.8 g (0.13 oz)

Turn tube upside down

Twist until 5 pellets are dispensed

Remove cap and pour pellets under the tongue

Do not use if pellet dispenser seal is broken.

*CLAIMS BASED ON TRADITIONAL HOMEOPATHIC PRACTICE NOT ACCEPTED MEDICAL EVIDENCE. NOT FDA EVALUATED.
**C,K,CK, and X are homeopathic dilutions: see BoironUSA.com/info for details.

QUESTIONS

BoironUSA.com

Info@Boiron.com

1-800-264-7661

Made in France

Disbributed by

Boiron, Inc.

Newtown Square, PA

19073